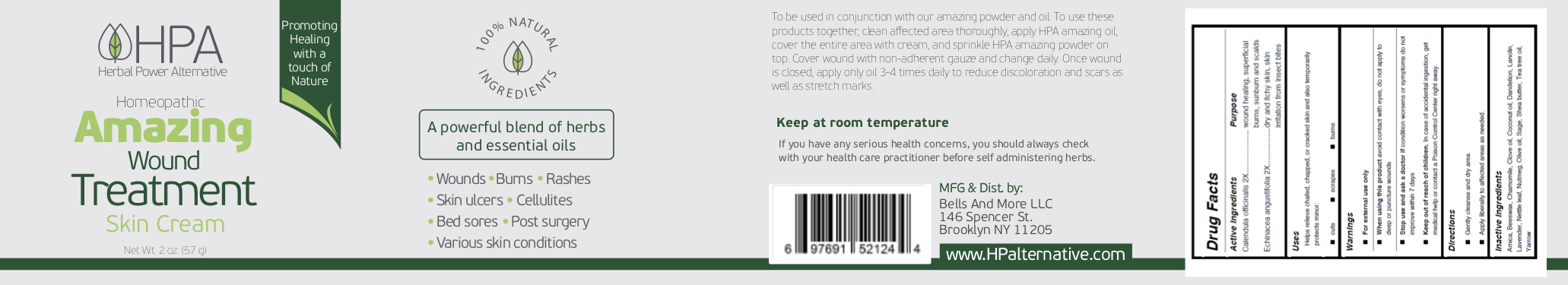 DRUG LABEL: Herbal Power Alternative
NDC: 81386-001 | Form: CREAM
Manufacturer: BELLS & MORE INC
Category: homeopathic | Type: HUMAN OTC DRUG LABEL
Date: 20210312

ACTIVE INGREDIENTS: ECHINACEA ANGUSTIFOLIA 2 [hp_X]/57 g; CALENDULA OFFICINALIS FLOWER 2 [hp_X]/57 g
INACTIVE INGREDIENTS: OLIVE OIL; TEA TREE OIL; CHAMOMILE; SAGE; SHEA BUTTER; ARNICA MONTANA; NUTMEG; ACHILLEA MILLEFOLIUM OIL; PEG-8 BEESWAX; COCONUT OIL; TARAXACUM OFFICINALE; LANOLIN; CLOVE OIL; URTICA DIOICA LEAF; LAVENDER OIL

HPA Homeopathic Cream

Active Ingredients

Calendula officinalis 2X

Echinacea angustifolia 2X

Purpose

Calendula officinalis: wound healing, superficial burns, sunburn and scalds

Echinacea angustifolia: dry and itchy skin, skin irritation from insect bites

Uses

Helps relieve chafed, chapped, or cracked skin and also temporarily protects minor:

- cuts
- scrapes
- burns

Warnings

For external use only

When using this product avoid contact with eyes, do not apply to deep or puncture wounds

Stop use and ask a doctor if condition worsens or symptoms do not improve within 7 days

Keep out of reach of children. In case of accidental ingestion, get medical help or contact a Poison Control Center right away.

Directions

- Gently cleanse and dry area.
- Apply liberally to affected areas as needed.

Inactive Ingredients

Arnica, Beeswax, Chamomile, Clove oil, Coconut oil, Dandelion, Lanolin, Lavender, Nettle leaf, Nutmeg, Olive oil, Sage, Shea butter, Tea tree oil, Yarrow

Principal Display Panel

57 g NDC: 81386-001-57